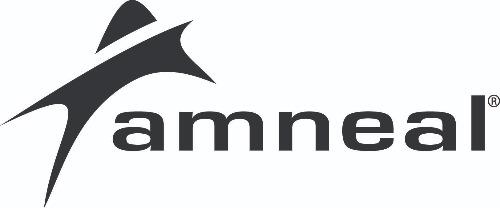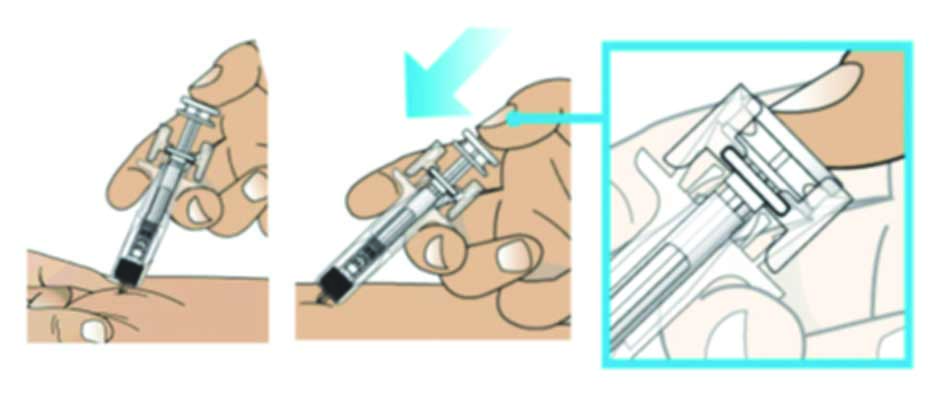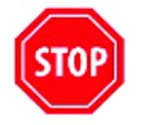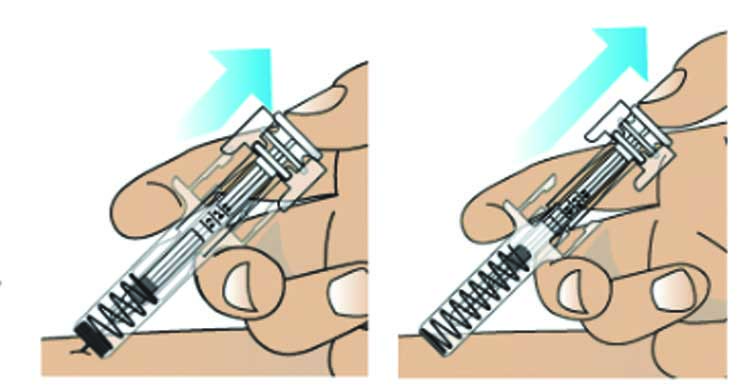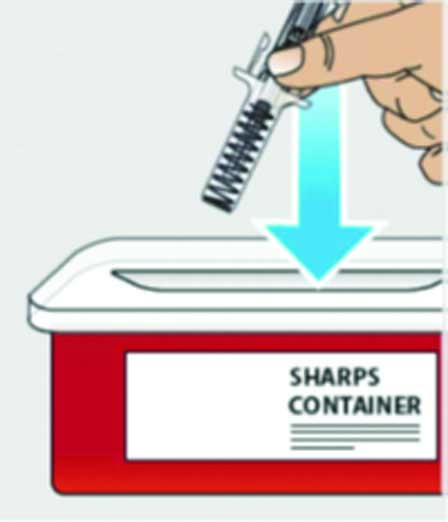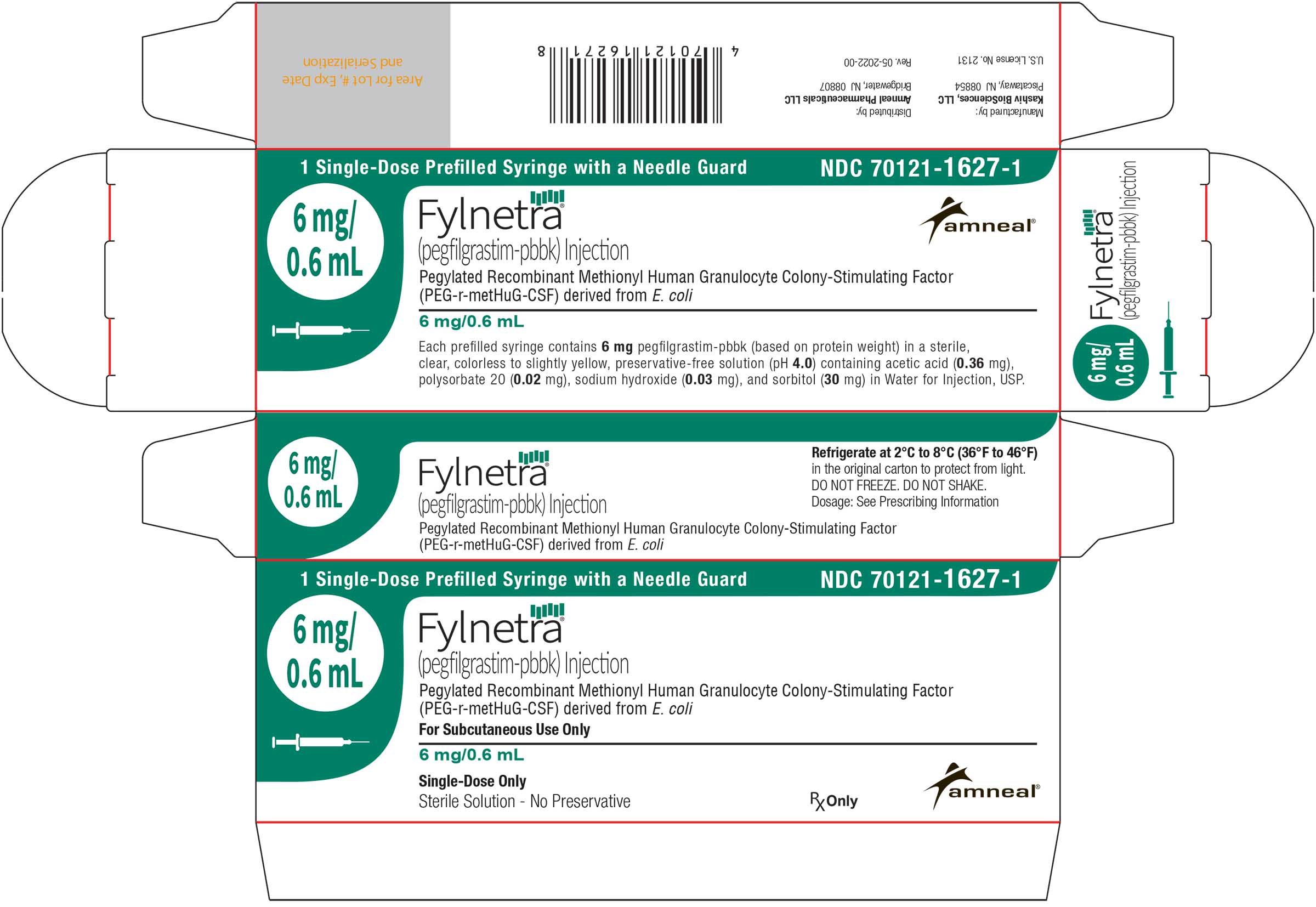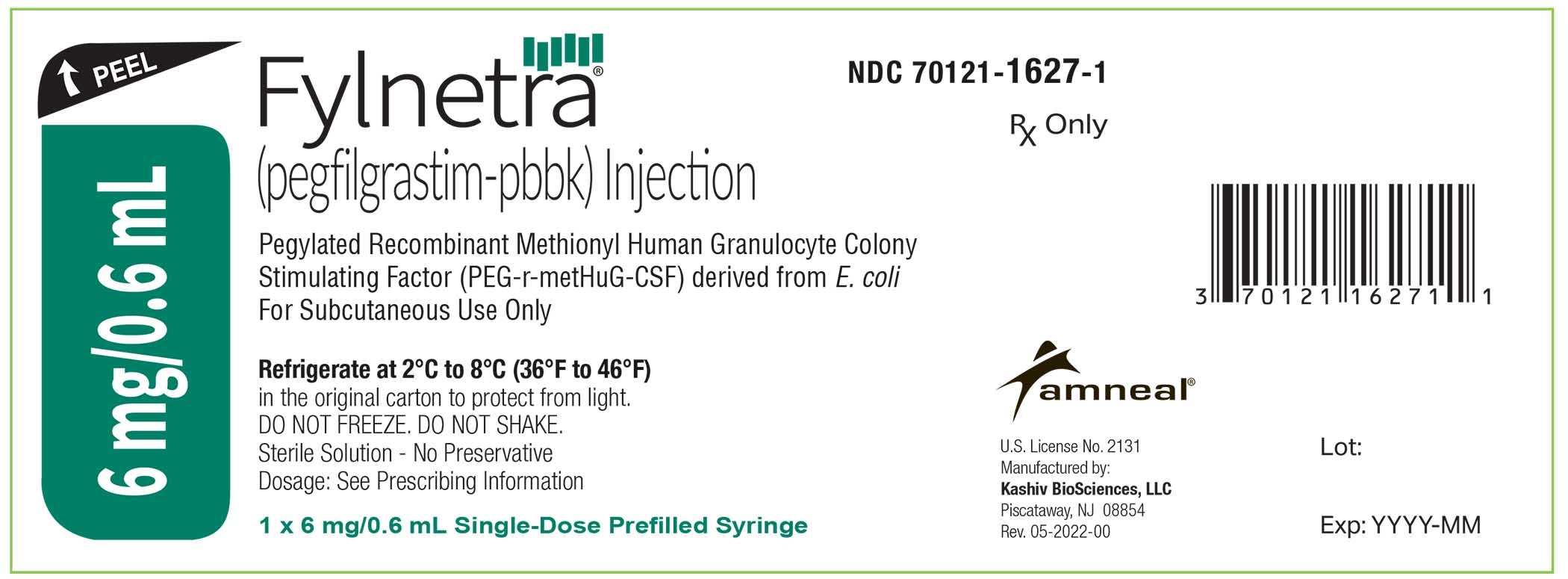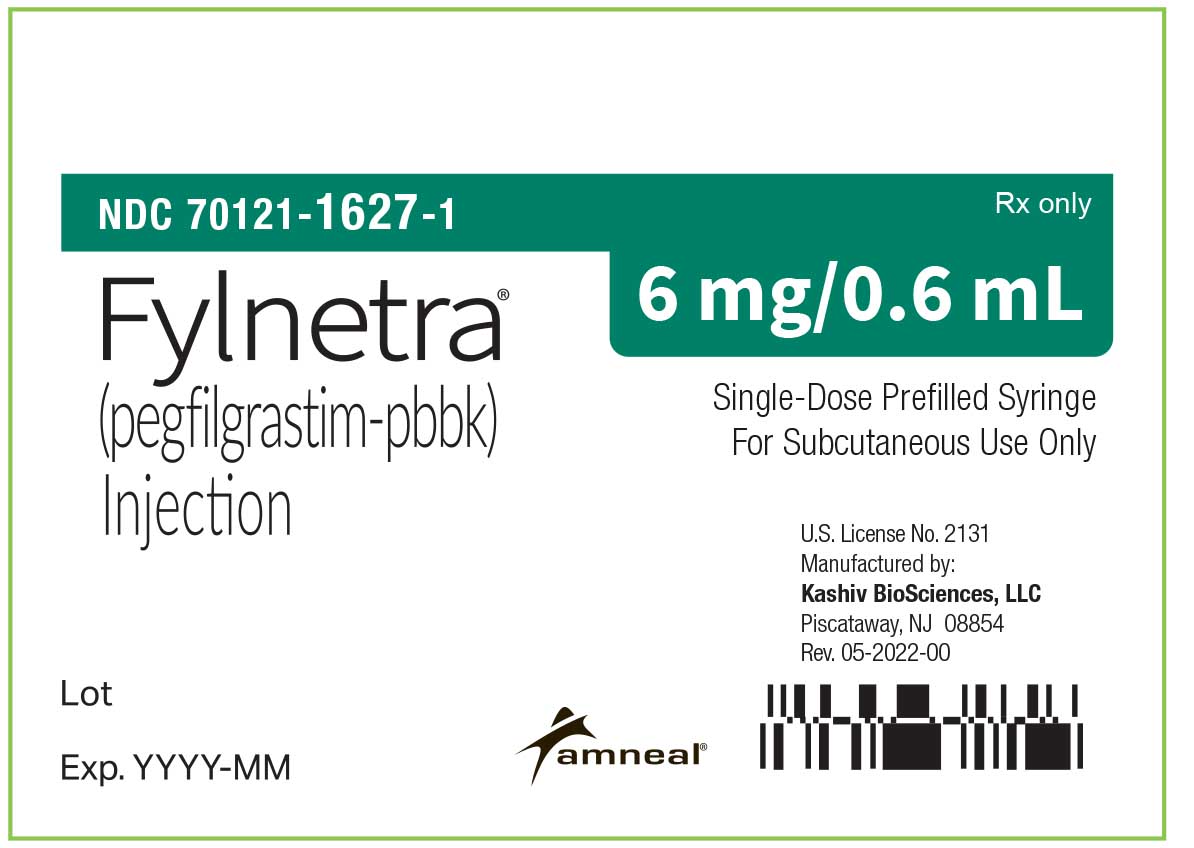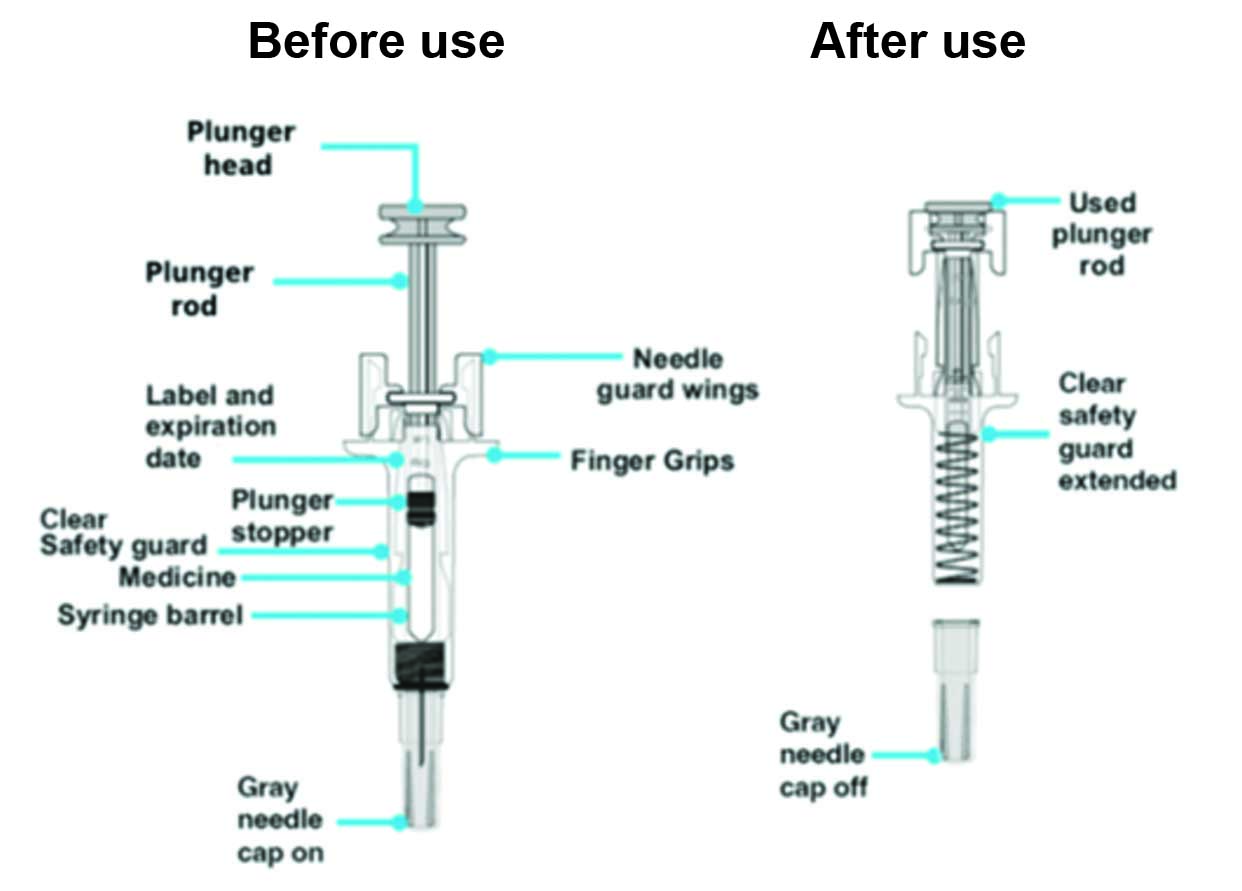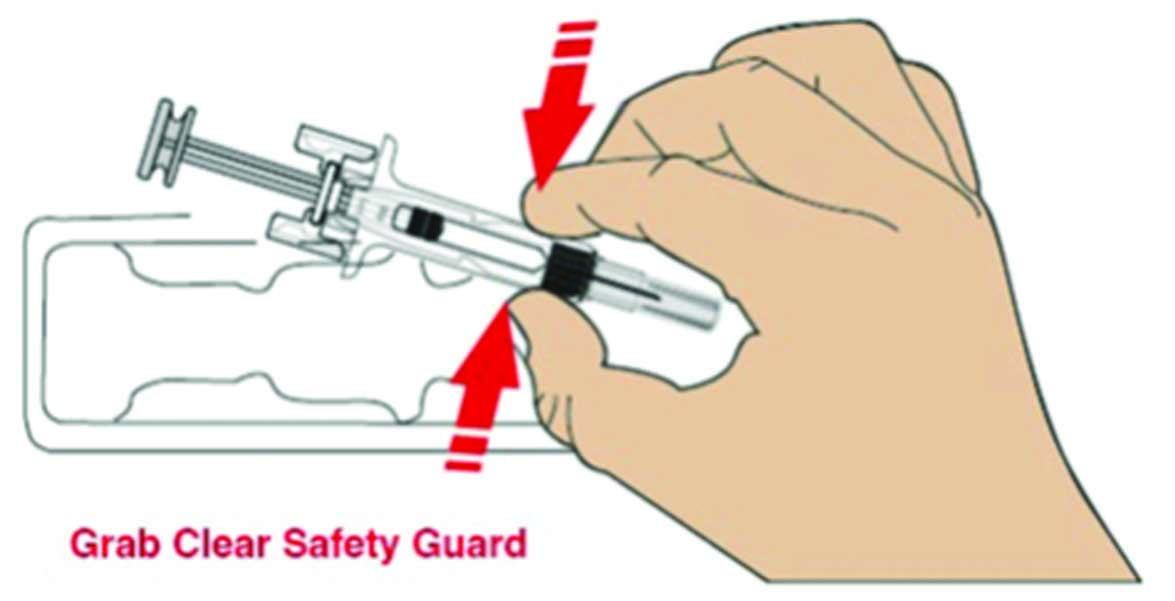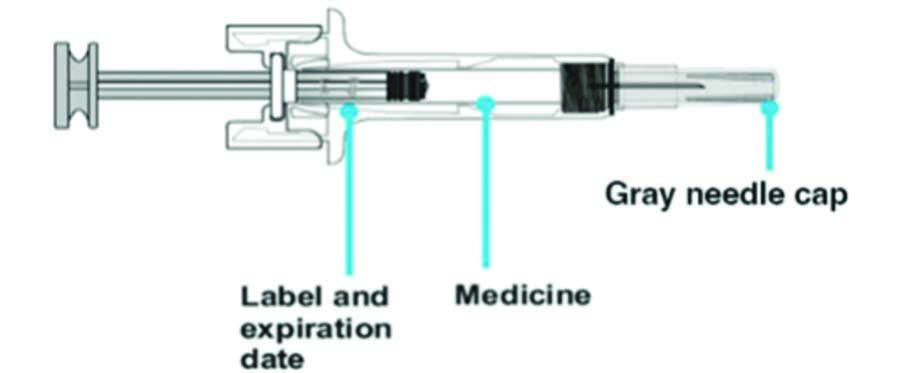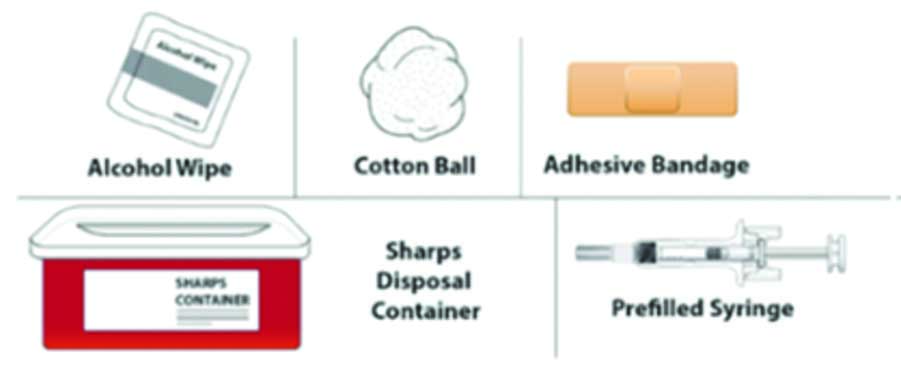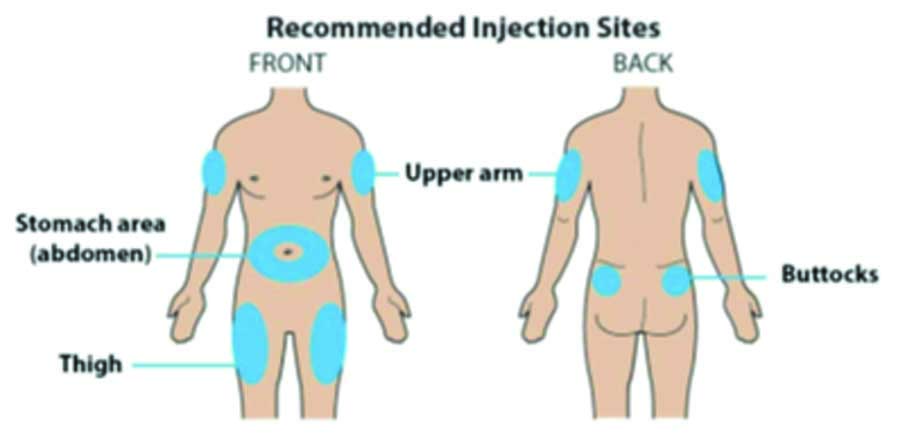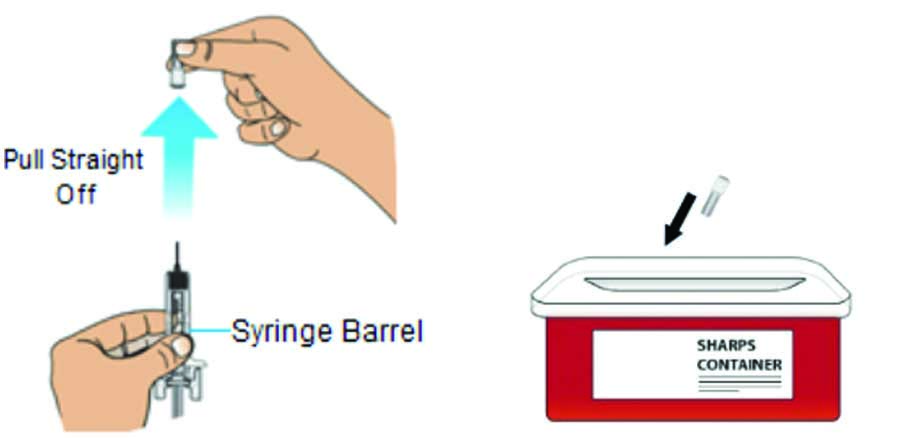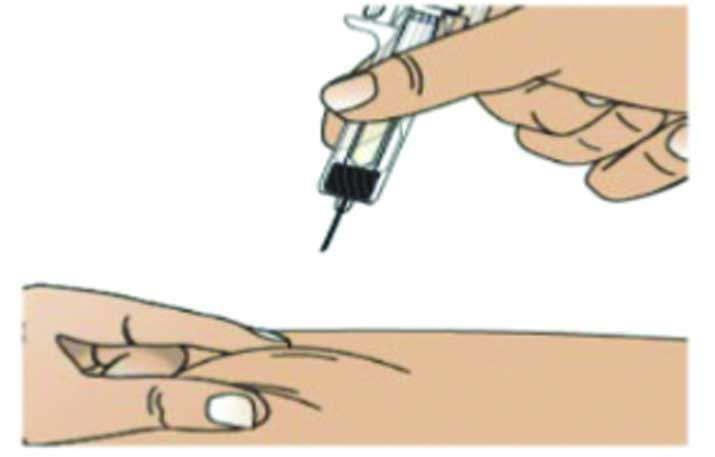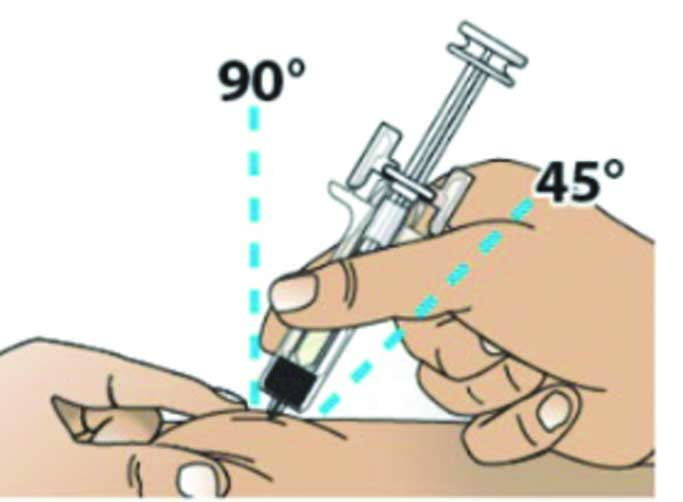 DRUG LABEL: FYLNETRA
NDC: 70121-1627 | Form: INJECTION
Manufacturer: Amneal Pharmaceuticals LLC
Category: prescription | Type: HUMAN PRESCRIPTION DRUG LABEL
Date: 20250425

ACTIVE INGREDIENTS: PEGFILGRASTIM 6 mg/0.6 mL
INACTIVE INGREDIENTS: ACETIC ACID 0.36 mg/0.6 mL; SORBITOL 30 mg/0.6 mL; POLYSORBATE 20 0.02 mg/0.6 mL; SODIUM HYDROXIDE 0.03 mg/0.6 mL; WATER

HIGHLIGHTS OF PRESCRIBING INFORMATION

These highlights do not include all the information needed to use FYLNETRA safely and effectively. See full prescribing information for FYLNETRA.
FYLNETRA® (pegfilgrastim-pbbk) injection, for subcutaneous use
Initial U.S. Approval: 2022
FYLNETRA (pegfilgrastim-pbbk) is biosimilar* to NEULASTA (pegfilgrastim).

RECENT MAJOR CHANGES

Indications and Usage, Patients with Hematopoietic Subsyndrome of Acute Radiation Syndrome (1.2) 04/2025

Dosage and Administration, Patients with Hematopoietic Subsyndrome of Acute Radiation Syndrome (2.2) 04/2025

1 INDICATIONS AND USAGE

FYLNETRA is a leukocyte growth factor indicated to

- decrease the incidence of infection, as manifested by febrile neutropenia, in patients with non-myeloid malignancies receiving myelosuppressive anti-cancer drugs associated with a clinically significant incidence of febrile neutropenia. (1.1)

- Increase survival in patients acutely exposed to myelosuppressive doses of radiation (Hematopoietic Subsyndrome of Acute Radiation Syndrome). (1.2)

Limitations of Use

FYLNETRA is not indicated for the mobilization of peripheral blood progenitor cells for hematopoietic stem cell transplantation.

2 DOSAGE AND ADMINISTRATION

Patients with cancer receiving myelosuppressive chemotherapy

- 6 mg administered subcutaneously once per chemotherapy cycle. (2.1)
- Do not administer between 14 days before and 24 hours after administration of cytotoxic chemotherapy. (2.1)
- Use weight based dosing for pediatric patients weighing less than 45 kg; refer to Table 1. (2.3)

Patients acutely exposed to myelosuppressive doses of radiation

- Two doses, 6 mg each, administered subcutaneously one week apart. Administer the first dose as soon as possible after suspected or confirmed exposure to myelosuppressive doses of radiation, and a second dose one week after. (2.2)
- Use weight based dosing for pediatric patients weighing less than 45 kg; refer to Table 1. (2.3)

3 DOSAGE FORMS AND STRENGTHS

Injection: 6 mg/0.6 mL solution in a single-dose prefilled syringe for manual use only. (3)

4 CONTRAINDICATIONS

Patients with a history of serious allergic reactions to human granulocyte colony-stimulating factors such as pegfilgrastim products or filgrastim products. (4)

5 WARNINGS AND PRECAUTIONS

- Fatal splenic rupture: Evaluate patients who report left upper abdominal or shoulder pain for an enlarged spleen or splenic rupture.(5.1)
- Acute respiratory distress syndrome (ARDS): Evaluate patients who develop fever, lung infiltrates, or respiratory distress. Discontinue FYLNETRA in patients with ARDS. (5.2)
- Serious allergic reactions, including anaphylaxis: Permanently discontinue FYLNETRA in patients with serious allergic reactions. (5.3)
- Fatal sickle cell crises: Discontinue FYLNETRA if sickle cell crisis occurs. (5.4)
- Glomerulonephritis: Evaluate and consider dose-reduction or interruption of FYLNETRA if causality is likely. (5.5)
- Thrombocytopenia: Monitor platelet counts. (5.7)
- Myelodysplastic Syndrome (MDS) and Acute Myeloid Leukemia (AML): Monitor patients with breast and lung cancer using FYLNETRA in conjunction with chemotherapy and/or radiotherapy for signs and symptoms of MDS/AML. (5.10)

6 ADVERSE REACTIONS

Most common adverse reactions (≥ 5% difference in incidence compared to placebo) are bone pain and pain in extremity. (6.1)

To report SUSPECTED ADVERSE REACTIONS, contact Amneal Pharmaceuticals LLC at 1-877-835 5472, option 3 or FDA at 1-800-FDA-1088 or www.fda.gov/medwatch.

* Biosimilar means that the biological product is approved based on data demonstrating that it is highly similar to an FDA-approved biological product, known as a reference product, and that there are no clinically meaningful differences between the biosimilar product and the reference product. Biosimilarity of FYLNETRA® has been demonstrated for the condition(s) of use (e.g. indication(s), dosing regimen(s)), strength(s), dosage form(s), and route(s) of administration described in its Full Prescribing Information.

FULL PRESCRIBING INFORMATION

1 INDICATIONS AND USAGE

1.1 Patients with Cancer Receiving Myelosuppressive Chemotherapy

FYLNETRA is indicated to decrease the incidence of infection, as manifested by febrile neutropenia, in patients with non-myeloid malignancies receiving myelosuppressive anti-cancer drugs associated with a clinically significant incidence of febrile neutropenia [see Clinical Studies (14.1)].

Limitations of Use

FYLNETRA is not indicated for the mobilization of peripheral blood progenitor cells for hematopoietic stem cell transplantation.

1.2 Patients with Hematopoietic Subsyndrome of Acute Radiation Syndrome

FYLNETRA is indicated to increase survival in patients acutely exposed to myelosuppressive doses of radiation [see Dosage and Administration (2.2) and Clinical Studies (14.2)].

2 DOSAGE AND ADMINISTRATION

2.1 Patients with Cancer Receiving Myelosuppressive Chemotherapy

The recommended dosage of FYLNETRA is a single subcutaneous injection of 6 mg administered once per chemotherapy cycle. For dosing in pediatric patients weighing less than 45 kg, refer to Table 1. Do not administer FYLNETRA between 14 days before and 24 hours after administration of cytotoxic chemotherapy.

2.2 Patients with Hematopoietic Subsyndrome of Acute Radiation Syndrome

The recommended dose of FYLNETRA is two doses, 6 mg each, administered subcutaneously one week apart. For dosing in pediatric patients weighing less than 45 kg, refer to Table 1. Administer the first dose as soon as possible after suspected or confirmed exposure to radiation levels greater than 2 gray (Gy). Administer the second dose one week after the first dose.

Obtain a baseline complete blood count (CBC). Do not delay administration of FYLNETRA if a CBC is not readily available. Estimate a patient’s absorbed radiation dose (i.e., level of radiation exposure) based on information from public health authorities, biodosimetry if available, or clinical findings such as time to onset of vomiting or lymphocyte depletion kinetics.

2.3 Administration

FYLNETRA is administered subcutaneously via a single-dose prefilled syringe for manual use.

Prior to use‚ remove the carton from the refrigerator and allow the FYLNETRA prefilled syringe to reach room temperature for a minimum of 30 minutes. Discard any prefilled syringe left at room temperature for greater than 72 hours.

Parenteral drug products should be inspected visually for particulate matter and discoloration prior to administration, whenever solution and container permit. Do not administer FYLNETRA if discoloration or particulates are observed.

The needle cap on the prefilled syringe is not made with natural rubber latex.

Pediatric Patients weighing less than 45 kg

The FYLNETRA prefilled syringe is not designed to allow for direct administration of doses less than 0.6 mL (6 mg). The syringe does not bear graduation marks, which are necessary to accurately measure doses of FYLNETRA less than 0.6 mL (6 mg) for direct administration to patients. Thus, the direct administration to patients requiring dosing of less than 0.6 mL (6 mg) is not recommended due to the potential for dosing errors. Refer to Table 1.

Table 1. Dosing of FYLNETRA for pediatric patients weighing less than 45 kg

Body Weight | FYLNETRA Dose | Volume to Administer
Less than 10 kg* | See below* | See below*
10 to 20 kg | 1.5 mg | 0.15 mL
21 to 30 kg | 2.5 mg | 0.25 mL
31 to 44 kg | 4 mg | 0.4 mL

*For pediatric patients weighing less than 10 kg, administer 0.1 mg/kg (0.01 mL/kg) of FYLNETRA.

3 DOSAGE FORMS AND STRENGTHS

FYLNETRA is a clear, colorless to slightly yellow, preservative-free solution available as:

- Injection: 6 mg/0.6 mL in a single-dose prefilled syringe for manual use only.

4 CONTRAINDICATIONS

FYLNETRA is contraindicated in patients with a history of serious allergic reactions to pegfilgrastim products or filgrastim products. Reactions have included anaphylaxis [see Warnings and Precautions (5.3)].

5 WARNINGS AND PRECAUTIONS

5.1 Splenic Rupture

Splenic rupture, including fatal cases, can occur following the administration of pegfilgrastim products. Evaluate for an enlarged spleen or splenic rupture in patients who report left upper abdominal or shoulder pain after receiving FYLNETRA.

5.2 Acute Respiratory Distress Syndrome

Acute respiratory distress syndrome (ARDS) can occur in patients receiving pegfilgrastim products. Evaluate patients who develop fever and lung infiltrates or respiratory distress after receiving FYLNETRA, for ARDS. Discontinue FYLNETRA in patients with ARDS.

5.3 Serious Allergic Reactions

Serious allergic reactions, including anaphylaxis, can occur in patients receiving pegfilgrastim products. The majority of reported events occurred upon initial exposure. Allergic reactions, including anaphylaxis, can recur within days after the discontinuation of initial anti-allergic treatment. Permanently discontinue FYLNETRA in patients with serious allergic reactions. Do not administer FYLNETRA to patients with a history of serious allergic reactions to pegfilgrastim products or filgrastim products.

5.4 Use in Patients with Sickle Cell Disorders

Severe and sometimes fatal sickle cell crises can occur in patients with sickle cell disorders receiving pegfilgrastim products. Discontinue FYLNETRA if sickle cell crisis occurs.

5.5 Glomerulonephritis

Glomerulonephritis has occurred in patients receiving pegfilgrastim products. The diagnoses were based upon azotemia, hematuria (microscopic and macroscopic), proteinuria, and renal biopsy. Generally, events of glomerulonephritis resolved after dose-reduction or discontinuation of pegfilgrastim products. If glomerulonephritis is suspected, evaluate for cause. If causality is likely, consider dose-reduction or interruption of FYLNETRA.

5.6 Leukocytosis

White blood cell (WBC) counts of 100 x 10^9/L or greater have been observed in patients receiving pegfilgrastim products. Monitoring of complete blood count (CBC) during FYLNETRA therapy is recommended.

5.7 Thrombocytopenia

Thrombocytopenia has been reported in patients receiving pegfilgrastim products. Monitor platelet counts.

5.8 Capillary Leak Syndrome

Capillary leak syndrome has been reported after G-CSF administration, including pegfilgrastim products, and is characterized by hypotension, hypoalbuminemia, edema and hemoconcentration. Episodes vary in frequency, severity and may be life-threatening if treatment is delayed. Patients who develop symptoms of capillary leak syndrome should be closely monitored and receive standard symptomatic treatment, which may include a need for intensive care.

5.9 Potential for Tumor Growth Stimulatory Effects on Malignant Cells

The granulocyte colony-stimulating factor (G-CSF) receptor through which pegfilgrastim products and filgrastim products act has been found on tumor cell lines. The possibility that pegfilgrastim products act as a growth factor for any tumor type, including myeloid malignancies and myelodysplasia, diseases for which pegfilgrastim products are not approved, cannot be excluded.

5.10 Myelodysplastic Syndrome (MDS) and Acute Myeloid Leukemia (AML) in Patients with Breast and Lung Cancer

MDS and AML have been associated with the use of pegfilgrastim products in conjunction with chemotherapy and/or radiotherapy in patients with breast and lung cancer. Monitor patients for signs and symptoms of MDS/AML in these settings.

5.11 Aortitis

Aortitis has been reported in patients receiving pegfilgrastim products. It may occur as early as the first week after start of therapy. Manifestations may include generalized signs and symptoms such as fever, abdominal pain, malaise, back pain, and increased inflammatory markers (e.g., c-reactive protein and white blood cell count). Consider aortitis in patients who develop these signs and symptoms without known etiology. Discontinue FYLNETRA if aortitis is suspected.

5.12 Nuclear Imaging

Increased hematopoietic activity of the bone marrow in response to growth factor therapy has been associated with transient positive bone imaging changes. This should be considered when interpreting bone imaging results.

6 ADVERSE REACTIONS

The following clinically significant adverse reactions are discussed in greater detail in other sections of the labeling:

- Splenic Rupture [see Warnings and Precautions (5.1)]
- Acute Respiratory Distress Syndrome [see Warnings and Precautions (5.2)]
- Serious Allergic Reactions [see Warnings and Precautions (5.3)]
- Use in Patients with Sickle Cell Disorders [see Warnings and Precautions (5.4)]
- Glomerulonephritis [see Warnings and Precautions (5.5)]
- Leukocytosis [see Warnings and Precautions (5.6)]
- Thrombocytopenia [see Warnings and Precautions (5.7)]
- Capillary Leak Syndrome [see Warnings and Precautions (5.8)]
- Potential for Tumor Growth Stimulatory Effects on Malignant Cells [see Warnings and Precautions (5.9)]
- Myelodysplastic Syndrome [see Warnings and Precautions (5.10)]
- Acute Myeloid Leukemia [see Warnings and Precautions (5.10)]
- Aortitis [see Warnings and Precautions (5.11)]

6.1 Clinical Trials Experience

Because clinical trials are conducted under widely varying conditions, adverse reaction rates observed in the clinical trials of a drug cannot be directly compared with rates in the clinical trials of another drug and may not reflect the rates observed in clinical practice.

Pegfilgrastim clinical trials safety data are based upon 932 patients receiving pegfilgrastim in seven randomized clinical trials. The population was 21 to 88 years of age and 92% female. The ethnicity was 75% Caucasian, 18% Hispanic, 5% Black, and 1% Asian. Patients with breast (n = 823), lung and thoracic tumors (n = 53) and lymphoma (n = 56) received pegfilgrastim after nonmyeloablative cytotoxic chemotherapy. Most patients received a single 100 mcg/kg (n = 259) or a single 6 mg (n = 546) dose per chemotherapy cycle over 4 cycles.

The following adverse reaction data in Table 2 are from a randomized, double-blind, placebo-controlled study in patients with metastatic or non-metastatic breast cancer receiving docetaxel 100 mg/m^2 every 21 days (Study 3). A total of 928 patients were randomized to receive either 6 mg pegfilgrastim (n = 467) or placebo (n = 461). The patients were 21 to 88 years of age and 99% female. The ethnicity was 66% Caucasian, 31% Hispanic, 2% Black, and < 1% Asian, Native American, or other.

The most common adverse reactions occurring in ≥ 5% of patients and with a between-group difference of ≥ 5% higher in the pegfilgrastim arm in placebo-controlled clinical trials are bone pain and pain in extremity.

Table 2. Adverse Reactions with ≥ 5% Higher Incidence in pegfilgrastim Patients Compared to Placebo in Study 3

Body System; Adverse Reaction | Placebo; (N= 461) | Pegfilgrastim 6 mg SC on Day 2; (N= 467)
Musculoskeletal and connective tissue disorders
Bone pain | 26% | 31%
Pain in extremity | 4% | 9%

Leukocytosis

In clinical studies, leukocytosis (WBC counts > 100 x 10^9/L) was observed in less than 1% of 932 patients with non-myeloid malignancies receiving pegfilgrastim. No complications attributable to leukocytosis were reported in clinical studies.

6.2 Immunogenicity

The observed incidence of anti-drug antibodies is highly dependent on the sensitivity and specificity of the assay. Differences in assay methods preclude meaningful comparisons of the incidence of anti-drug antibodies in the studies described below with the incidence of anti-drug antibodies in other studies, including those of pegfilgrastim or of other pegfilgrastim products.

Binding antibodies to pegfilgrastim were detected using a BIAcore assay. The approximate limit of detection for this assay is 500 ng/mL. Pre-existing binding antibodies were detected in approximately 6% (51/849) of patients with metastatic breast cancer. Four of 521 pegfilgrastim-treated subjects who were negative at baseline developed binding antibodies to pegfilgrastim following treatment. None of these 4 patients had evidence of neutralizing antibodies detected using a cell-based bioassay.

6.3 Postmarketing Experience

The following adverse reactions have been identified during post approval use of pegfilgrastim products. Because these reactions are reported voluntarily from a population of uncertain size, it is not always possible to reliably estimate their frequency or establish a causal relationship to drug exposure.

- Splenic rupture and splenomegaly (enlarged spleen) [see Warnings and Precautions (5.1)]
- Acute respiratory distress syndrome (ARDS) [see Warnings and Precautions (5.2)]
- Allergic reactions/hypersensitivity, including anaphylaxis, skin rash, urticaria, generalized erythema, and flushing [see Warnings and Precautions (5.3)]
- Sickle cell crisis [see Warnings and Precautions (5.4)]
- Glomerulonephritis [see Warnings and Precautions (5.5)]
- Leukocytosis [see Warnings and Precautions (5.6)]
- Thrombocytopenia [see Warnings and Precautions (5.7)]
- Capillary Leak Syndrome [see Warnings and Precautions (5.8)]
- Injection site reactions
- Sweet’s syndrome (acute febrile neutrophilic dermatosis), cutaneous vasculitis
- Myelodysplastic syndrome (MDS) and acute myeloid leukemia (AML) in patients with breast and lung cancer receiving chemotherapy and/or radiotherapy [see Warnings and Precautions (5.10)]
- Aortitis [see Warnings and Precautions (5.11)]
- Alveolar hemorrhage

USE IN SPECIFIC POPULATIONS

8.1 Pregnancy

Risk Summary

Although available data with FYLNETRA or pegfilgrastim product use in pregnant women are insufficient to establish whether there is a drug associated risk of major birth defects, miscarriage, or adverse maternal or fetal outcomes, there are available data from published studies in pregnant women exposed to filgrastim products. These studies have not established an association of filgrastim product use during pregnancy with major birth defects, miscarriage, or adverse maternal or fetal outcomes.

In animal studies, no evidence of reproductive/developmental toxicity occurred in the offspring of pregnant rats that received cumulative doses of pegfilgrastim approximately 10 times the recommended human dose (based on body surface area). In pregnant rabbits, increased embryolethality and spontaneous abortions occurred at 4 times the maximum recommended human dose simultaneously with signs of maternal toxicity (see Data).

The estimated background risk of major birth defects and miscarriage for the indicated population is unknown. All pregnancies have a background risk of birth defect, loss, or other adverse outcomes. In the U.S. general population, the estimated background risks of major birth defects and miscarriage in clinically recognized pregnancies is 2% to 4% and 15% to 20%, respectively.

Data

Animal Data

Pregnant rabbits were dosed with pegfilgrastim subcutaneously every other day during the period of organogenesis. At cumulative doses ranging from the approximate human dose to approximately 4 times the recommended human dose (based on body surface area), the treated rabbits exhibited decreased maternal food consumption, maternal weight loss, as well as reduced fetal body weights and delayed ossification of the fetal skull; however, no structural anomalies were observed in the offspring from either study. Increased incidences of post-implantation losses and spontaneous abortions (more than half the pregnancies) were observed at cumulative doses approximately 4 times the recommended human dose, which were not seen when pregnant rabbits were exposed to the recommended human dose.

Three studies were conducted in pregnant rats dosed with pegfilgrastim at cumulative doses up to approximately 10 times the recommended human dose at the following stages of gestation: during the period of organogenesis, from mating through the first half of pregnancy, and from the first trimester through delivery and lactation. No evidence of fetal loss or structural malformations was observed in any study. Cumulative doses equivalent to approximately 3 and 10 times the recommended human dose resulted in transient evidence of wavy ribs in fetuses of treated mothers (detected at the end of gestation but no longer present in pups evaluated at the end of lactation).

8.2 Lactation

Risk Summary

There are no data on the presence of pegfilgrastim products in human milk, the effects on the breastfed child, or the effects on milk production. Other filgrastim products are secreted poorly into breast milk, and filgrastim products are not absorbed orally by neonates. The developmental and health benefits of breastfeeding should be considered along with the mother’s clinical need for FYLNETRA and any potential adverse effects on the breastfed child from FYLNETRA or from the underlying maternal condition.

8.4 Pediatric Use

The safety and effectiveness of FYLNETRA have been established in pediatric patients. No overall differences in safety were identified between adult and pediatric patients based on postmarketing surveillance and review of the scientific literature.

Use of FYLNETRA in pediatric patients for chemotherapy-induced neutropenia is based on adequate and well-controlled studies of pegfilgrastim in adults with additional pharmacokinetic and safety data of pegfilgrastim in pediatric patients with sarcoma [see Clinical Pharmacology (12.3) andClinical Studies (14.1)].

The use of FYLNETRA to increase survival in pediatric patients acutely exposed to myelosuppressive doses of radiation is based on efficacy studies of pegfilgrastim conducted in animals and clinical data supporting the use of pegfilgrastim in patients with cancer receiving myelosuppressive chemotherapy. Efficacy studies of pegfilgrastim products could not be conducted in humans with acute radiation syndrome for ethical and feasibility reasons. Results from population modeling and simulation indicate that two doses of pegfilgrastim (Table 1), administered one week apart provide pediatric patients with exposures comparable to that in adults receiving two 6 mg doses one week apart [see Dosage and Administration (2.3), Clinical Pharmacology (12.3) and Clinical Studies (14.2)].

8.5 Geriatric Use

Of the 932 patients with cancer who received pegfilgrastim in clinical studies, 139 (15%) were aged 65 and over, and 18 (2%) were aged 75 and over. No overall differences in safety or effectiveness were observed between patients aged 65 and older and younger patients.

10 OVERDOSAGE

Overdosage of pegfilgrastim products may result in leukocytosis and bone pain. Events of edema, dyspnea, and pleural effusion have been reported in a single patient who administered pegfilgrastim on 8 consecutive days in error. In the event of overdose, the patient should be monitored for adverse reactions [see Adverse Reactions (6)].

11 DESCRIPTION

Pegfilgrastim-pbbk is a covalent conjugate of recombinant methionyl human G-CSF and monomethoxypolyethylene glycol. Recombinant methionyl human G-CSF is a water-soluble 175 amino acid protein with a molecular weight of approximately 19 kilodaltons (kD). Recombinant methionyl human G-CSF is obtained from the bacterial fermentation of a strain of E coli transformed with a genetically engineered plasmid containing the human G-CSF gene. To produce pegfilgrastim-pbbk, a 20 kD monomethoxypolyethylene glycol molecule is covalently bound to the N-terminal methionyl residue of recombinant methionyl human G-CSF. The average molecular weight of pegfilgrastim-pbbk is approximately 39 kD. Kanamycin is used during the manufacturing process but is undetectable in the final product.

FYLNETRA (pegfilgrastim-pbbk) injection is supplied in 0.6 mL prefilled syringes for manual subcutaneous injection. The prefilled syringe does not bear graduation marks and is designed to deliver the entire contents of the syringe (6 mg/0.6 mL).

The delivered 0.6 mL dose from the prefilled syringe contains 6 mg pegfilgrastim-pbbk (based on protein weight) in a sterile, clear, colorless to slightly yellow, preservative-free solution (pH 4.0) containing acetic acid (0.36 mg), polysorbate 20 (0.02 mg), sodium hydroxide (0.03 mg), and sorbitol (30 mg) in Water for Injection, USP.

12 CLINICAL PHARMACOLOGY

12.1 Mechanism of Action

Pegfilgrastim products are colony-stimulating factors that act on hematopoietic cells by binding to specific cell surface receptors, thereby stimulating proliferation, differentiation, commitment, and end cell functional activation.

12.2 Pharmacodynamics

Animal data and clinical data in humans suggest a correlation between pegfilgrastim products’ exposure and the duration of severe neutropenia as a predictor of efficacy. Selection of the dosing regimen of FYLNETRA is based on reducing the duration of severe neutropenia.

12.3 Pharmacokinetics

The pharmacokinetics of pegfilgrastim was studied in 379 patients with cancer. The pharmacokinetics of pegfilgrastim was nonlinear, and clearance decreased with increases in dose. Neutrophil receptor binding is an important component of the clearance of pegfilgrastim, and serum clearance is directly related to the number of neutrophils. In addition to numbers of neutrophils, body weight appeared to be a factor. Patients with higher body weights experienced higher systemic exposure to pegfilgrastim after receiving a dose normalized for body weight. A large variability in the pharmacokinetics of pegfilgrastim was observed. The half-life of pegfilgrastim ranged from 15 to 80 hours after subcutaneous injection.

Specific Populations

No gender-related differences were observed in the pharmacokinetics of pegfilgrastim, and no differences were observed in the pharmacokinetics of geriatric patients (≥ 65 years of age) compared with younger patients (< 65 years of age) [see Use in Specific Populations (8.5)].

Renal Impairment

In a study of 30 subjects with varying degrees of renal dysfunction, including end stage renal disease, renal dysfunction had no effect on the pharmacokinetics of pegfilgrastim.

Pediatric Patients with Cancer Receiving Myelosuppressive Chemotherapy

The pharmacokinetics and safety of pegfilgrastim were studied in 37 pediatric patients with sarcoma in Study 4 [see Clinical Studies (14.1)]. The mean (± standard deviation [SD]) systemic exposure (AUC0-inf) of pegfilgrastim after subcutaneous administration at 100 mcg/kg was 47.9 (± 22.5) mcg.hr/mL in the youngest age group (0 to 5 years, n = 11), 22.0 (± 13.1) mcg·hr/mL in the 6 to 11 years age group (n = 10), and 29.3 (± 23.2) mcg·hr/mL in the 12 to 21 years age group (n = 13). The terminal elimination half-lives of the corresponding age groups were 30.1 (± 38.2) hours, 20.2 (± 11.3) hours, and 21.2 (± 16.0) hours, respectively.

Patients Acutely Exposed to Myelosuppressive Doses of Radiation

The pharmacokinetics of pegfilgrastim products is not available in patients acutely exposed to myelosuppressive doses of radiation. Based on limited pharmacokinetic data in irradiated non-human primates, the area under the concentration-time curve (AUC), reflecting the exposure to pegfilgrastim in non-human primates following a 300 mcg/kg dose of pegfilgrastim, appears to be greater than in humans receiving a 6 mg dose. Results from population modeling and simulation indicate that two 6 mg doses of pegfilgrastim administered one week apart in adults result in clinically relevant effects on duration of grade 3 and 4 neutropenia. In addition, weight based dosing in pediatric patients weighing less than 45 kg [see Dosage and Administration, Section 2.3, Table 1] provides exposures comparable to those in adults receiving two 6 mg doses one week apart.

13 NONCLINICAL TOXICOLOGY

13.1 Carcinogenesis, Mutagenesis, Impairment of Fertility

No carcinogenicity or mutagenesis studies have been performed with pegfilgrastim products.

Pegfilgrastim did not affect reproductive performance or fertility in male or female rats at cumulative weekly doses approximately 6 to 9 times higher than the recommended human dose (based on body surface area).

14 CLINICAL STUDIES

14.1 Patients with Cancer Receiving Myelosuppressive Chemotherapy

Pegfilgrastim was evaluated in three randomized, double-blind, controlled studies. Studies 1 and 2 were active-controlled studies that employed doxorubicin 60 mg/m^2 and docetaxel 75 mg/m^2 administered every 21 days for up to 4 cycles for the treatment of metastatic breast cancer. Study 1 investigated the utility of a fixed dose of pegfilgrastim. Study 2 employed a weight-adjusted dose. In the absence of growth factor support, similar chemotherapy regimens have been reported to result in a 100% incidence of severe neutropenia (ANC < 0.5 x 10^9/L) with a mean duration of 5 to 7 days and a 30% to 40% incidence of febrile neutropenia. Based on the correlation between the duration of severe neutropenia and the incidence of febrile neutropenia found in studies with filgrastim, duration of severe neutropenia was chosen as the primary endpoint in both studies, and the efficacy of pegfilgrastim was demonstrated by establishing comparability to filgrastim-treated patients in the mean days of severe neutropenia.

In Study 1, 157 patients were randomized to receive a single subcutaneous injection of pegfilgrastim (6 mg) on day 2 of each chemotherapy cycle or daily subcutaneous filgrastim (5 mcg/kg/day) beginning on day 2 of each chemotherapy cycle. In Study 2, 310 patients were randomized to receive a single subcutaneous injection of pegfilgrastim (100 mcg/kg) on day 2 or daily subcutaneous filgrastim (5 mcg/kg/day) beginning on day 2 of each chemotherapy cycle.

Both studies met the major efficacy outcome measure of demonstrating that the mean days of severe neutropenia of pegfilgrastim-treated patients did not exceed that of filgrastim-treated patients by more than 1 day in cycle 1 of chemotherapy. The mean days of cycle 1 severe neutropenia in Study 1 were 1.8 days in the pegfilgrastim arm compared to 1.6 days in the filgrastim arm [difference in means 0.2 (95% CI - 0.2, 0.6)] and in Study 2 were 1.7 days in the pegfilgrastim arm compared to 1.6 days in the filgrastim arm [difference in means 0.1 (95% CI - 0.2, 0.4)].

A secondary endpoint in both studies was days of severe neutropenia in cycles 2 through 4 with results similar to those for cycle 1.

Study 3 was a randomized, double-blind, placebo-controlled study that employed docetaxel 100 mg/m^2 administered every 21 days for up to 4 cycles for the treatment of metastatic or non-metastatic breast cancer. In this study, 928 patients were randomized to receive a single subcutaneous injection of pegfilgrastim (6 mg) or placebo on day 2 of each chemotherapy cycle. Study 3 met the major trial outcome measure of demonstrating that the incidence of febrile neutropenia (defined as temperature ≥ 38.2°C and ANC ≤ 0.5 x 10^9/L) was lower for pegfilgrastim-treated patients as compared to placebo-treated patients (1% versus 17%, respectively, p < 0.001). The incidence of hospitalizations (1% versus 14%) and IV anti-infective use (2% versus 10%) for the treatment of febrile neutropenia was also lower in the pegfilgrastim-treated patients compared to the placebo-treated patients.

Study 4 was a multicenter, randomized, open-label study to evaluate the efficacy, safety, and pharmacokinetics [see Clinical Pharmacology (12.3)] of pegfilgrastim in pediatric and young adult patients with sarcoma. Patients with sarcoma receiving chemotherapy age 0 to 21 years were eligible. Patients were randomized to receive subcutaneous pegfilgrastim as a single-dose of 100 mcg/kg (n = 37) or subcutaneous filgrastim at a dose 5 mcg/kg/day (n = 6) following myelosuppressive chemotherapy. Recovery of neutrophil counts was similar in the pegfilgrastim and filgrastim groups. The most common adverse reaction reported was bone pain.

14.2 Patients with Hematopoietic Subsyndrome of Acute Radiation Syndrome

Efficacy studies of pegfilgrastim products could not be conducted in humans with acute radiation syndrome for ethical and feasibility reasons. Approval of this indication was based on efficacy studies conducted in animals and data supporting pegfilgrastim’s effect on severe neutropenia in patients with cancer receiving myelosuppressive chemotherapy [see Dosage and Administration (2.1)].

The recommended dose of FYLNETRA is two doses, 6 mg each, administered one week apart for humans exposed to myelosuppressive doses of radiation. For pediatric patients weighing less than 45 kg, dosing of FYLNETRA is weight based and is provided in Table 1 [see Dosage and Administration (2.3)]. This dosing regimen is based on population modeling and simulation analyses. The exposure associated with this dosing regimen is expected to provide sufficient pharmacodynamic activity to treat humans exposed to myelosuppressive doses of radiation [see Clinical Pharmacology (12.3)]. The safety of pegfilgrastim at a dose of 6 mg has been assessed on the basis of clinical experience in patients with cancer receiving myelosuppressive chemotherapy.

The efficacy of pegfilgrastim for the acute radiation syndrome setting was studied in a randomized, placebo-controlled non-human primate model of radiation injury. Rhesus macaques were randomized to either a control (n = 23) or treated (n = 23) cohort. On study day 0, animals (n = 6 to 8 per irradiation day) were exposed to total body irradiation (TBI) of 7.50 ± 0.15 Gy delivered at 0.8 ± 0.03 Gy/min, representing a dose that would be lethal in 50% of animals by 60 days of follow-up (LD50/60). Animals were administered subcutaneous injections of a blinded treatment (control article [5% dextrose in water] or pegfilgrastim [300-319 mcg/kg/day]) on study day 1 and on study day 8. The primary endpoint was survival. Animals received medical management consisting of intravenous fluids, antibiotics, blood transfusions, and other support as required.

Pegfilgrastim significantly (at 0.0014 level of significance) increased 60-day survival in irradiated non-human primates: 91% survival (21/23) in the pegfilgrastim group compared to 48% survival (11/23) in the control group.

16 HOW SUPPLIED/STORAGE AND HANDLING

FYLNETRA single-dose prefilled syringe for manual use

FYLNETRA (pegfilgrastim-pbbk) injection is a clear, colorless to slightly yellow, preservative-free solution supplied in a prefilled single-dose syringe for manual use containing 6 mg pegfilgrastim-pbbk, supplied with a 27-gauge, 1/2-inch needle with an UltraSafe PlusTM Passive Needle Guard.

The needle cap on the prefilled syringe is not made with natural rubber latex.

FYLNETRA is provided in a dispensing pack containing one sterile 6 mg/0.6 mL prefilled syringe (NDC 70121-1627-1).

FYLNETRA prefilled syringe does not bear graduation marks and is intended only to deliver the entire contents of the syringe (6 mg/0.6 mL) for direct administration. Use of the prefilled syringe is not recommended for direct administration for pediatric patients weighing less than 45 kg who require doses that are less than the full contents of the syringe.

Store refrigerated between 36°F to 46°F (2°C to 8°C) in the carton to protect from light. Do not shake. Discard syringes stored at room temperature [68°F to 77°F (20°C to 25°C)] for more than 72 hours. Avoid freezing; if frozen, thaw in the refrigerator before administration. Discard syringe if frozen more than once.

17 PATIENT COUNSELING INFORMATION

Advise the patient to read the FDA-approved patient labeling (Patient Information and Instructions for Use).

Advise patients of the following risks and potential risks with FYLNETRA:

- Splenic rupture and splenomegaly
- Acute Respiratory Distress Syndrome
- Serious allergic reactions
- Sickle cell crisis
- Glomerulonephritis
- Increased risk of Myelodysplastic Syndrome and/or Acute Myeloid Leukemia in patients with breast and lung cancer who receive FYLNETRA in conjunction with chemotherapy and/or radiation therapy
- Capillary Leak Syndrome
- Aortitis

Advise patients acutely exposed to myelosuppressive doses of radiation (Hematopoietic Subsyndrome of Acute Radiation Syndrome) that efficacy studies of pegfilgrastim products for this indication could not be conducted in humans for ethical and feasibility reasons and that, therefore, approval of this use was based on efficacy studies conducted in animals [see Clinical Studies (14.2)].

Instruct patients who self-administer FYLNETRA using the single-dose prefilled syringe of the:

- Importance of following the Instructions for Use.
- Dangers of reusing syringes.
- Importance of following local requirements for proper disposal of used syringes.

Manufactured by:

Kashiv BioSciences, LLC

Piscataway, NJ 08854

US License No. 2131

Distributed by:

Amneal Pharmaceuticals LLC

Bridgewater, NJ 08807

Rev. 04-2025-02

LBL-0003

PATIENT INFORMATION

FYLNETRA® (fil-ne-trah)

(pegfilgrastim-pbbk)

injection

Single-Dose Prefilled Syringe

What is FYLNETRA?

FYLNETRA is a man-made form of granulocyte colony-stimulating factor (G-CSF). G-CSF is a substance produced by the body. It stimulates the growth of neutrophils, a type of white blood cell important in the body’s fight against infection.

Acute Radiation Syndrome: The effectiveness of pegfilgrastim for this use was only studied in animals, because it could not be studied in people.

Do not take FYLNETRA if you have had a serious allergic reaction to pegfilgrastim products or filgrastim products.

Before you receive FYLNETRA, tell your healthcare provider about all of your medical conditions, including if you:

- have a sickle cell disorder.
- have kidney problems.
- are pregnant or plan to become pregnant. It is not known if FYLNETRA will harm your unborn baby.
- are breastfeeding or plan to breastfeed. It is not known if FYLNETRA passes into your breast milk.

Tell your healthcare provider about all of the medicines you take, including prescription and over-the-counter medicines, vitamins, and herbal supplements.

How will I receive FYLNETRA?

- FYLNETRA is given as an injection under your skin (subcutaneous injection) by a healthcare provider. If your healthcare provider decides that the subcutaneous injections can be given at home by you or your caregiver, follow the detailed “Instructions for Use” that comes with your FYLNETRA for information on how to prepare and inject a dose of FYLNETRA.
- You and your caregiver will be shown how to prepare and inject FYLNETRA before you use it.
- You should not inject a dose of FYLNETRA to children weighing less than 45 kg from a FYLNETRA prefilled syringe. A dose less than 0.6 mL (6 mg) cannot be accurately measured using the FYLNETRA prefilled syringe.
- If you are receiving FYLNETRA because you are also receiving chemotherapy, the last dose of FYLNETRA should be injected at least 14 days before and 24 hours after your dose of chemotherapy.
- If you miss a dose of FYLNETRA, talk to your healthcare provider about when you should give your next dose.

What are the possible side effects of FYLNETRA?

FYLNETRA may cause serious side effects, including:

- Spleen rupture. Your spleen may become enlarged and can rupture. A ruptured spleen can cause death. Call your healthcare provider right away if you have pain in the left upper stomach area or your left shoulder.
- A serious lung problem called Acute Respiratory Distress Syndrome (ARDS). Call your healthcare provider or get emergency help right away if you have shortness of breath with or without a fever, trouble breathing, or a fast rate of breathing.
- Serious allergic reactions. FYLNETRA can cause serious allergic reactions. These reactions can cause a rash over your whole body, shortness of breath, wheezing, dizziness, swelling around your mouth or eyes, fast heart rate, and sweating. If you have any of these symptoms, stop using FYLNETRA and call your healthcare provider or get emergency medical help right away.
- Sickle cell crises. You may have a serious sickle cell crisis, which could lead to death, if you have a sickle cell disorder and receive FYLNETRA. Call your healthcare provider right away if you have symptoms of sickle cell crisis such as pain or difficulty breathing.
- Kidney injury (glomerulonephritis). FYLNETRA can cause kidney injury. Call your healthcare provider right away if you develop any of the following symptoms.

- swelling of your face or ankles
- blood in your urine or dark colored urine
- you urinate less than usual

- Increased white blood cell count (leukocytosis). Your healthcare provider will check your blood during treatment with FYLNETRA.
- Decreased platelet count (thrombocytopenia). Your healthcare provider will check your blood during treatment with FYLNETRA. Tell your healthcare provider if you have unusual bleeding or bruising during treatment with FYLNETRA. This could be a sign of decreased platelet counts, which may reduce the ability of your blood to clot.
- Capillary Leak Syndrome. FYLNETRA can cause fluid to leak from blood vessels into your body’s tissues. This condition is called “Capillary Leak Syndrome” (CLS). CLS can quickly cause you to have symptoms that may become life-threatening. Get emergency medical help right away if you develop any of the following symptoms:

- swelling or puffiness and are urinating less than usual
- trouble breathing
- swelling of your stomach area (abdomen) and feeling of fullness
- dizziness or feeling faint
- a general feeling of tiredness

- Myelodysplastic syndrome and acute myeloid leukemia. If you have breast cancer or lung cancer, when FYLNETRA is used with chemotherapy and radiation therapy, or with radiation therapy alone, you may have an increased risk of developing a precancerous blood condition called myelodysplastic syndrome (MDS) or a blood cancer called acute myeloid leukemia (AML). Symptoms of MDS and AML may include tiredness, fever, and easy bruising or bleeding. Call your healthcare provider if you develop these symptoms during treatment with FYLNETRA.
- Inflammation of the aorta (aortitis). Inflammation of the aorta (the large blood vessel which transports blood from the heart to the body) has been reported in patients who received pegfilgrastim products. Symptoms may include fever, abdominal pain, feeling tired, and back pain. Call your healthcare provider if you experience these symptoms.

The most common side effects of FYLNETRA are pain in the bones, arms, and legs.

These are not all the possible side effects of FYLNETRA.

Call your healthcare provider for medical advice about side effects. You may report side effects to FDA at 1-800-FDA-1088.

How should I store FYLNETRA?

- Store FYLNETRA in the refrigerator between 36°F to 46°F (2°C to 8°C).
- Do not freeze. If FYLNETRA is accidentally frozen, allow the prefilled syringe to thaw in the refrigerator before injecting.
- Do not use a FYLNETRA prefilled syringe that has been frozen more than 1 time. Use a new FYLNETRA prefilled syringe.
- Keep the prefilled syringe in the original carton to protect from light or physical damage.
- Do not shake the prefilled syringe.
- Take FYLNETRA out of the refrigerator 30 minutes before use and allow it to reach room temperature before preparing an injection.
- Throw away (dispose of) any FYLNETRA that has been left at room temperature, 68°F to 77°F (20°C to 25°C), for more than 72 hours.

Keep the FYLNETRA prefilled syringe out of the reach of children.

General information about the safe and effective use of FYLNETRA.

Medicines are sometimes prescribed for purposes other than those listed in a Patient Information leaflet. Do not use FYLNETRA for a condition for which it was not prescribed. Do not give FYLNETRA to other people, even if they have the same symptoms that you have. It may harm them. You can ask your pharmacist or healthcare provider for information about FYLNETRA that is written for health professionals.

What are the ingredients in FYLNETRA?

Active ingredient: pegfilgrastim-pbbk

Inactive ingredients: acetic acid, polysorbate 20, sodium hydroxide and sorbitol in water for injection.

Manufactured by: Kashiv BioSciences, LLC, Piscataway, NJ 08854

US License No. 2131

Distributed by: Amneal Pharmaceuticals LLC, Bridgewater, NJ 08807

For more information, go to www.fylnetra.us or call 1-877-835-5472.

This Patient Information has been approved by the U.S. Food and Drug Administration. Rev. 04-2025-02

Instructions for Use

FYLNETRA® (fil-ne-trah)
(pegfilgrastim-pbbk)
Injection, for subcutaneous use
Single-Dose Prefilled Syringe

Guide to parts

Important: The needle is covered by the gray needle cap before use.

Important

Read the Patient Information for important information you need to know about FYLNETRA before using these Instructions for Use.

Before you use a FYLNETRA prefilled syringe, read this important information.

Storing the prefilled syringe

- Store FYLNETRA in the refrigerator between 36°F to 46°F (2°C to 8°C).
- Do not freeze.
- Keep the prefilled syringe in the original pack to protect from light or physical damage.
- Take the prefilled syringe out of the refrigerator 30 minutes before use and allow it to reach room temperature before preparing an injection.
- Throw away (dispose of) any FYLNETRA that has been at left at room temperature, 68°F to 77°F (20°C to 25°C), for more than 72 hours.
- Keep the FYLNETRA prefilled syringe out of the reach of children.

Using the prefilled syringe

- It is important that you do not try to give the injection unless you or your caregiver has received training from your healthcare provider.
- Make sure the name FYLNETRA appears on the pack and prefilled syringe label.
- Check the pack and prefilled syringe label to make sure the dose strength is 6 mg/0.6 mL.
- You should not inject a dose of FYLNETRA to children weighing less than 45 kg from a FYLNETRA prefilled syringe. A dose less than 0.6 mL (6 mg) cannot be accurately measured using the FYLNETRA prefilled syringe.
- Do not use a prefilled syringe after the expiration date on the label.
- Do not shake the prefilled syringe.
- Do not remove the gray needle cap from the prefilled syringe until you are ready to inject.
- Do not use the prefilled syringe if the pack is open or damaged.
- Do not use a prefilled syringe if it has been dropped on a hard surface. The prefilled syringe may be broken even if you cannot see the break. Use a new prefilled syringe.
- Do not attempt to activate the needle safety guard prior to injection.

Call your healthcare provider if you or your caregiver have any questions.

Step 1: Prepare

A. Remove the prefilled syringe pack from the refrigerator.

Put the original pack with any unused prefilled syringes back in the refrigerator.

Remove the syringe tray from the pack. On a clean, well-lit surface, place the syringe tray at room temperature for 30 minutes before you give an injection.

- Do not use the prefilled syringe if the pack is damaged.
- Do not try to warm the prefilled syringe by using a heat source such as hot water or microwave.
- Do not leave the prefilled syringe in direct sunlight.
- Do not shake the prefilled syringe.

Open the tray by peeling away the cover. Grab the clear safety guard to remove the prefilled syringe from the tray.

For safety reasons:

- Do not grab the plunger rod.
- Do not grab the gray needle cap.

B. Inspect the medicine and prefilled syringe.

Make sure the medicine in the prefilled syringe is clear and colorless.

- Do not use the prefilled syringe if:

- The medicine is cloudy or discolored, or contains flakes or particles
- Any part appears cracked or broken
- The prefilled syringe has been dropped
- The gray needle cap is missing or not securely attached.
- The expiration date printed on the label has passed.

In all cases, use a new prefilled syringe and call your healthcare provider.

C Gather all materials needed for the injection.

Wash your hands thoroughly with soap and water.

On a clean, well-lit work surface place the:

- Prefilled syringe
- Alcohol wipe
- Cotton ball or gauze pad
- Adhesive bandage
- Sharps disposal container

Step 2: Get ready

D Prepare and clean the injection site(s).

You can use:

- Thigh
- Stomach area (abdomen), except for a 2-inch area around the navel (belly button)
- Upper outer area of the buttocks (only if someone else is giving you the injection)
- Outer area of upper arm (only if someone else is giving you the injection)

Clean the injection site with an alcohol wipe. Let the skin dry.

- Do not touch this area again before injecting.
- If you want to use the same injection site, make sure it is not the same spot on the injection site you used for a previous injection.
- Do not inject into areas where the skin is tender, bruised, red, or hard. Avoid injecting into areas with scars or stretch marks.

E Hold the prefilled syringe by the barrel. Carefully pull the gray needle cap straight off and away from the body.

- Do not remove the gray needle cap from the prefilled syringe until you are ready to inject.
- Do not twist or bend the gray needle cap.
- Do not hold the prefilled syringe by the plunger rod.
- Do not put the gray needle cap back onto the prefilled syringe.

Important: Throw the gray needle cap into the sharps disposal container.

Step 3: Subcutaneous (under the skin) injection

F Pinch the injection site to create a firm surface.

Important: Keep skin pinched while injecting.

G Hold the pinch. Insert the needle into the skin at 45 to 90 degrees.

H Using slow and constant pressure, push the plunger rod until it reaches the bottom and the plunger head is completely between the needle guard wings.

Important: When you remove the syringe, if it looks like the medicine is still in the syringe barrel, this means you have not received a full dose. Call your healthcare provider right away.

Step 4: Finish

I Before you finish!

- While you continue to hold the syringe, slowly let go of the plunger head.
- As you let go of the plunger head, the needle will automatically slide into the clear safety guard until the needle is completely covered.

Important: If the clear safety guard does not activate after Step I, remove the needle from the skin and throw away (discard of) the used prefilled syringe as instructed in Step J right away.

Keep your hands away from the needle at all times.

J Discard (throw away) the used prefilled syringe

- Put the used prefilled syringe in a FDA-cleared sharps disposal container right away after use. Do not throw away (dispose of) the syringe in the household trash.
- If you do not have a FDA-cleared sharps disposal container, you may use a household container that is:

- made of a heavy-duty plastic,
- can be closed with a tight-fitting, puncture-resistant lid, without sharps being able to come out,
- upright and stable during use,
- leak-resistant, and
- properly labeled to warn of hazardous waste inside the container.

- When your sharps disposal container is almost full, you will need to follow your community guidelines for the right way to dispose of your sharps disposal container. There may be state or local laws about how you should throw away used needles and syringes. For more information about safe sharps disposal, and for specific information about sharps disposal in the state that you live in, go to the FDA’s website at http://www.fda.gov/safesharpsdisposal
- Do not reuse the prefilled syringe.
- Do not recycle the prefilled syringe or sharps disposal container or throw them into the household trash.

Important: Always keep the sharps disposal container out of the reach of children.

K Examine the injection site.

If there is blood, press a cotton ball or gauze pad on the injection site. Do not rub the injection site. Apply an adhesive bandage if needed.

This Instructions for Use has been approved by the U.S. Food and Drug Administration.

Manufactured by:

Kashiv BioSciences, LLC

Piscataway, NJ 08854

US License No. 2131

Distributed by:

Amneal Pharmaceuticals LLC

Bridgewater, NJ 08807

Rev. 05-2022-00